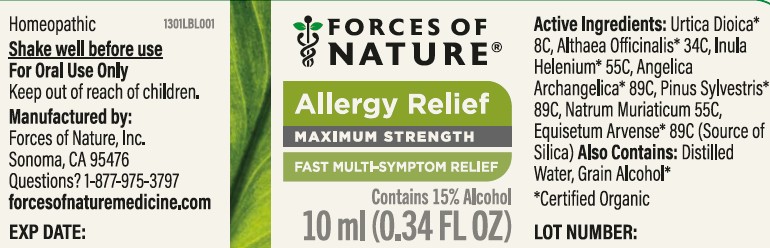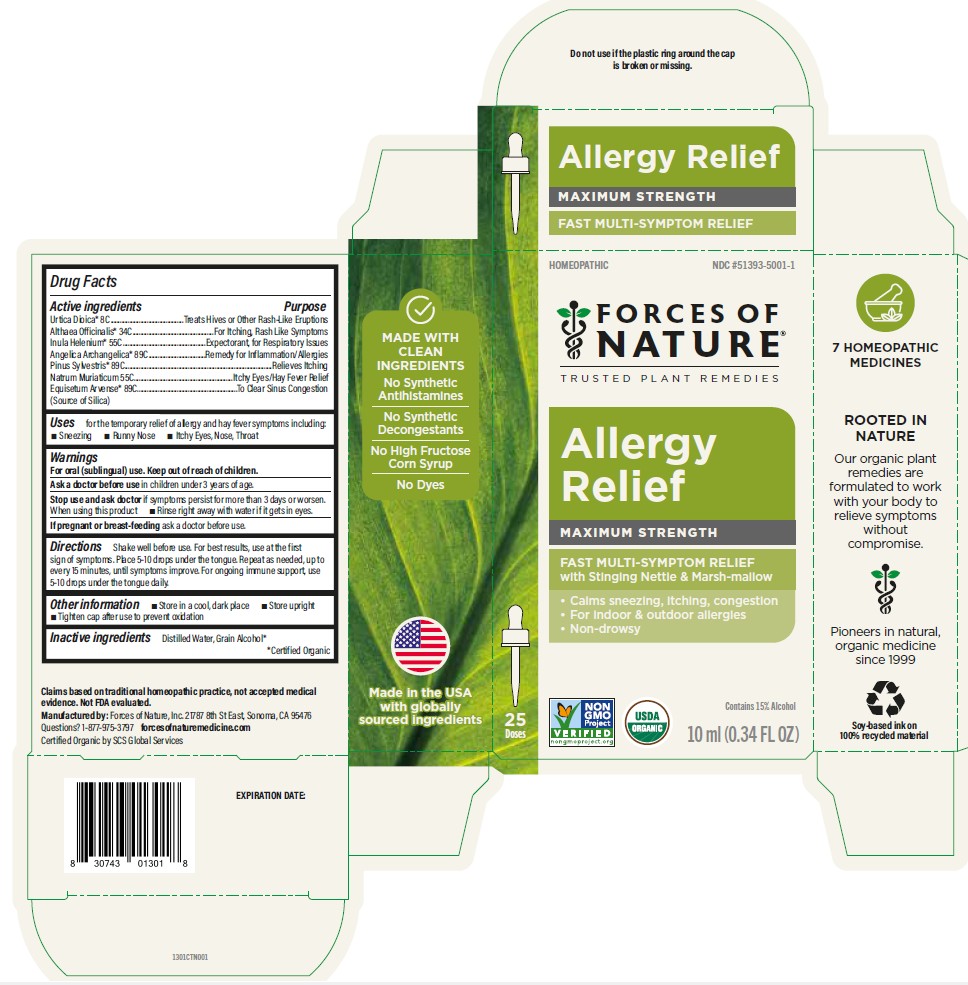 DRUG LABEL: Allergy
NDC: 51393-5001 | Form: SOLUTION/ DROPS
Manufacturer: Forces of Nature
Category: homeopathic | Type: HUMAN OTC DRUG LABEL
Date: 20260220

ACTIVE INGREDIENTS: URTICA DIOICA WHOLE 8 [hp_C]/100 mL; ALTHAEA OFFICINALIS ROOT 34 [hp_C]/100 mL; INULA HELENIUM ROOT 55 [hp_C]/100 mL; ANGELICA ARCHANGELICA ROOT 89 [hp_C]/100 mL; PINE NEEDLE OIL (PINUS SYLVESTRIS) 89 [hp_C]/100 mL; SODIUM CHLORIDE 55 [hp_C]/100 mL; SILICON DIOXIDE 89 [hp_C]/100 mL
INACTIVE INGREDIENTS: WATER; ALCOHOL

Allergy
Maximum Strength

Drug Facts

ACTIVE INGREDIENT

PURPOSE

Active ingredients
Urtica Dioica [Certified Organic] 8C | Treats Hives or Other Rash-Like Eruptions
Althaea Officinalis 34C | For Itching, Rash Like Symptoms
Inula Helenium 55C | Expectorant, for Respiratory Issues
Angelica Archangelica 89C | Remedy for Inflammation/Allergy Symptoms
Pinus Sylvestris 89C | Relieves Itching
Natrum Muriaticum 55C | Itchy Eyes/Hay Fever Relief
89C; (Source of Silica) | To Clear Sinus Congestion

Uses

For the temporary relief of allergy and hay fever symptoms including:

- Sneezing
- Runny Nose
- Itchy Eyes, Nose, Throat

Warnings

For oral (sublingual) use.

Ask a doctor before usein children under 3 years of age.

Stop use and ask doctorif symptoms persist for more than 3 days or worsen.

When using this product, rinse right away with water if it gets in the eyes.

PREGNANCY OR BREAST FEEDING

If pregnant or breast-feedingask a doctor before use.

Keep out of reach of children.

Directions

Shake well before use. For best results, use at the first sign of symptoms. Place 5-10 drops under the tongue. Repeat as needed, up to every 15 minutes until symptoms improve. For ongoing immune support, use 5 - 10 drops under the tongue daily.

Other information

- Store in a cool, dark place
- Store upright
- Tighten cap after use to prevent oxidation

Inactive ingredients

Distilled Water, Grain Alcohol

Questions or comments?

Call us at 1-877-975-3797 or visit our website www.forcesofnaturemedicine.com

Manufactured Distributed by
FORCES OF NATURE®
21787 8th St East, Sonoma, CA 95476 USA

PRINCIPAL DISPLAY PANEL - 10 ml Bottle Carton

Homeopathic
NDC #51393-5001-1

FORCES OF NATURE

Trusted Plant Remedies

Allergy Relief

MAXIMUM STRENGTH

FAST MULTI-SYMPTOM RELIEF
with Stinging Nettle & Marsh-mallow

• Calms sneezing, itching, congestion
• For indoor & outdoor allergies
• Non-drowsy

NON-GMO Project VERIFIED
nongmoproject.org

USDA ORGANIC

Contains 15% Alcohol

10 ml (.34 FL OZ)